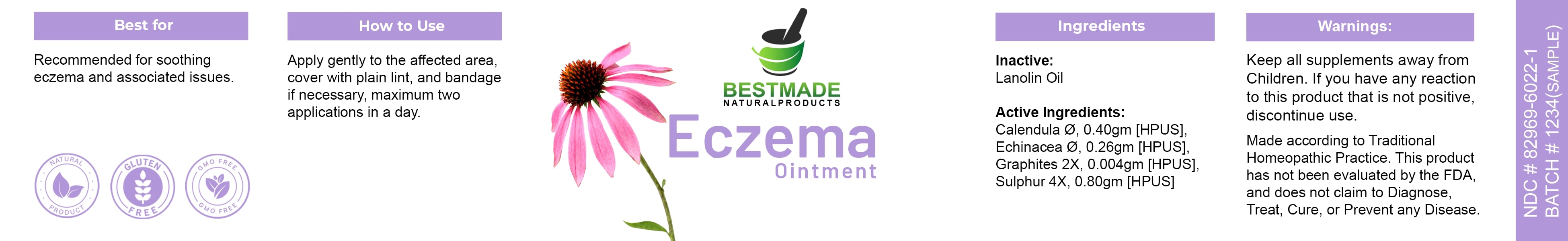 DRUG LABEL: Bestmade Natural Products Eczema
NDC: 82969-6022 | Form: OINTMENT
Manufacturer: Bestmade Natural Products
Category: homeopathic | Type: HUMAN OTC DRUG LABEL
Date: 20241218

ACTIVE INGREDIENTS: SULFUR 0.08 g/40 g; GRAPHITE 0.0004 g/40 g; CALENDULA OFFICINALIS WHOLE 0.4 g/40 g; ECHINACEA ANGUSTIFOLIA ROOT 0.26 g/40 g
INACTIVE INGREDIENTS: LANOLIN OIL 40 g/40 g

Eczema Ontment

DOSAGE AND ADMINISTRATION

How to Use

Apply gently to the affected area, cover with plain lint, and bandage if necessary, maximum two applications in a day.

INDICATIONS AND USAGE

Best for

Recommended for soothing eczema and associated issues.

PURPOSE

Best for

Recommended for soothing eczema and associated issues.

INACTIVE INGREDIENT

Ingredients

Inactive: Lanolin Oil

Active Ingredients:

Calendula 0.40gm [HPUS]

Echinacea 0.26gm [HPUS]

Graphites 2X, 0.004gm [HPUS]

Sulphur 4X, 0.80gm [HPUS]

Warnings:

Keep all supplements away from Children.

If you have any reaction to this product that is not positive, discontinue use.

Made according to Traditional Homeopathic Practice. This product has not been evaluated by the FDA, and does not claim to Diagnose, Treat, Cure, or Prevent any Disease.

Warnings:

Keep all supplements away from Children.

If you have any reaction to this product that is not positive, discontinue use.

Made according to Traditional Homeopathic Practice. This product has not been evaluated by the FDA, and does not claim to Diagnose, Treat, Cure, or Prevent any Disease.

Entire Package Label